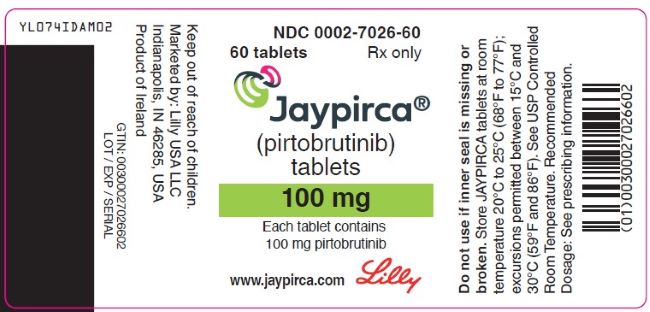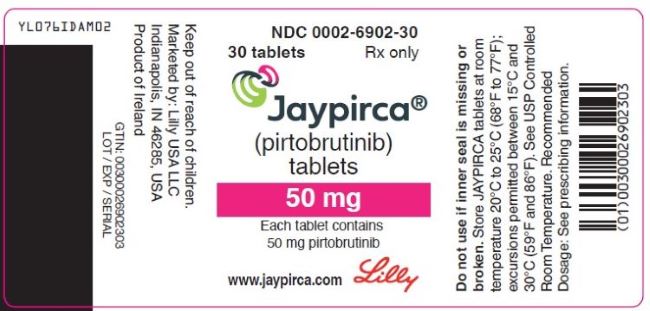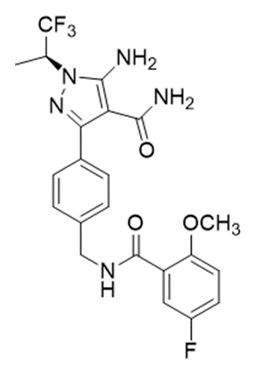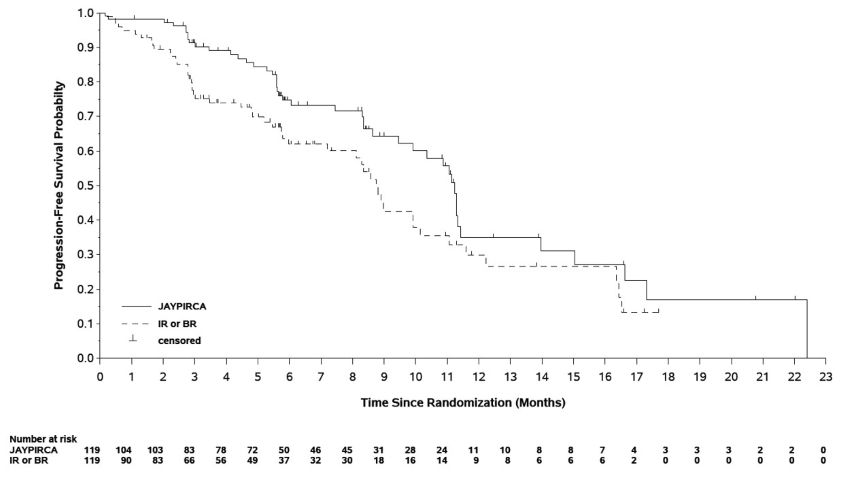 DRUG LABEL: JAYPIRCA
NDC: 0002-6902 | Form: TABLET, COATED
Manufacturer: Eli Lilly and Company
Category: prescription | Type: HUMAN PRESCRIPTION DRUG LABEL
Date: 20251204

ACTIVE INGREDIENTS: pirtobrutinib 50 mg/1 1
INACTIVE INGREDIENTS: hypromellose acetate succinate 12070923 (3 MPA.S); microcrystalline cellulose; lactose monohydrate; croscarmellose sodium; silicon dioxide; magnesium stearate; hypromellose, unspecified; titanium dioxide; triacetin; FD&C BLUE No. 2 Aluminum Lake

HIGHLIGHTS OF PRESCRIBING INFORMATION

These highlights do not include all the information needed to use JAYPIRCA safely and effectively. See full prescribing information for JAYPIRCA.
JAYPIRCA® (pirtobrutinib) tablets, for oral use
Initial U.S. Approval: 2023

RECENT MAJOR CHANGES

Indications and Usage, Chronic Lymphocytic Leukemia/Small Lymphocytic Lymphoma (1.2) | 12/2025

1 INDICATIONS AND USAGE

JAYPIRCA® is a kinase inhibitor indicated for the treatment of:

- Adult patients with relapsed or refractory mantle cell lymphoma (MCL) after at least two lines of systemic therapy, including a BTK inhibitor. (1.1).
  This indication is approved under accelerated approval based on response rate. Continued approval for this indication may be contingent upon verification and description of clinical benefit in a confirmatory trial.
- Adult patients with relapsed or refractory chronic lymphocytic leukemia or small lymphocytic lymphoma (CLL/SLL) who have previously been treated with a covalent BTK inhibitor. (1.2).

2 DOSAGE AND ADMINISTRATION

- Recommended dosage: 200 mg orally once daily; swallow whole with water, with or without food. Do not cut, crush, or chew tablets. (2.1)
- Manage toxicity using treatment interruption, dosage reduction, or discontinuation. (2.2)
- Reduce dose in patients with severe renal impairment. (2.3, 8.6)

3 DOSAGE FORMS AND STRENGTHS

Tablets: 50 mg, 100 mg (3).

4 CONTRAINDICATIONS

None (4).

5 WARNINGS AND PRECAUTIONS

- Infections: Monitor for signs and symptoms of infection, evaluate promptly, and treat. (5.1)
- Hemorrhage: Monitor for bleeding and manage appropriately. (5.2)
- Cytopenias: Monitor complete blood counts during treatment. (5.3)
- Cardiac Arrythmias: Monitor for symptoms of arrhythmias and manage appropriately. (5.4)
- Second Primary Malignancies: Other malignancies have developed, including skin cancers and other carcinomas. Monitor and advise patients to use sun protection. (5.5)
- Hepatotoxicity, Including Drug-Induced Liver Injury: Monitor hepatic function throughout treatment. (5.6)
- Embryo-Fetal Toxicity: Can cause fetal harm. Advise females of reproductive potential of potential risk to a fetus and to use effective contraception. (5.7, 8.1, 8.3)

6 ADVERSE REACTIONS

Most common adverse reactions (≥ 30%), including laboratory abnormalities, are fatigue, neutrophil count decreased, platelet count decreased, hemoglobin decreased, leukocytes decreased, lymphocyte count decreased and calcium decreased. (6.1)

To report SUSPECTED ADVERSE REACTIONS, contact Eli Lilly and Company at 1-800-LillyRx (1-800-545-5979) or FDA at 1-800-FDA-1088 or www.fda.gov/medwatch.

7 DRUG INTERACTIONS

- Strong CYP3A Inhibitors: Avoid concomitant use. If concomitant use is unavoidable, reduce the JAYPIRCA dose. (2.4, 7.1)
- Strong or Moderate CYP3A Inducers: Avoid concomitant use. If concomitant use of moderate CYP3A inducers is unavoidable, increase the JAYPIRCA dose. (2.5, 7.1)
- Sensitive CYP2C8, CYP2C19, CYP3A, P-gp, or BCRP Substrates: For substrates where minimal concentration changes may increase the risk of adverse reactions, follow recommendations for co-administration with CYP2C8, CYP2C19, CYP3A, P-gp, or BCRP inhibitors provided in their approved product labeling. (7.2)

8 USE IN SPECIFIC POPULATIONS

Lactation: Advise not to breastfeed (8.2)

FULL PRESCRIBING INFORMATION

1 INDICATIONS AND USAGE

1.1 Mantle Cell Lymphoma

JAYPIRCA® is indicated for the treatment of adult patients with relapsed or refractory mantle cell lymphoma (MCL) after at least two lines of systemic therapy, including a BTK inhibitor.

This indication is approved under accelerated approval based on response rate [see Clinical Studies (14.1)]. Continued approval for this indication may be contingent upon verification and description of clinical benefit in a confirmatory trial.

1.2 Chronic Lymphocytic Leukemia/Small Lymphocytic Lymphoma

JAYPIRCA is indicated for the treatment of adult patients with relapsed or refractory chronic lymphocytic leukemia or small lymphocytic lymphoma (CLL/SLL) who have previously been treated with a covalent BTK inhibitor.

2 DOSAGE AND ADMINISTRATION

2.1 Recommended Dosage

The recommended dosage of JAYPIRCA is 200 mg orally once daily until disease progression or unacceptable toxicity.

Advise patients of the following:

- Swallow tablets whole with water. Do not cut, crush, or chew tablets.
- Take JAYPIRCA at the same time each day. JAYPIRCA may be taken with or without food.
- If a dose of JAYPIRCA is missed by more than 12 hours, do not make up the dose and take the next dose as scheduled.

2.2 Dosage Modifications for Adverse Reactions

Recommended dosage modifications of JAYPIRCA for adverse reactions are presented in Table 1 [see Warnings and Precautions (5.1, 5.2, 5.3, and 5.4)].

Table 1: Recommended Dosage Modification of JAYPIRCA for Adverse Reactions
Adverse Reaction | Occurrences Requiring Dosage Modification | Modification (Starting Dosage: 200 mg once daily)
- Grade 3 or greater non-hematologic toxicity a - Absolute neutrophil count < 1 to 0.5 x 10^9/L with fever and/or infection - Absolute neutrophil count < 0.5 x 10^9/L lasting 7 or more days - Platelet count < 50 to 25 x 10^9/L with bleeding - Platelet count < 25 x 10^9/L | First occurrence | Interrupt JAYPIRCA until recovery to Grade 1 or baseline; restart at original dosage (200 mg once daily)a.
- Grade 3 or greater non-hematologic toxicity a - Absolute neutrophil count < 1 to 0.5 x 10^9/L with fever and/or infection - Absolute neutrophil count < 0.5 x 10^9/L lasting 7 or more days - Platelet count < 50 to 25 x 10^9/L with bleeding - Platelet count < 25 x 10^9/L | Second occurrence | Interrupt JAYPIRCA until recovery to Grade 1 or baseline; restart at 100 mg once daily.
- Grade 3 or greater non-hematologic toxicity a - Absolute neutrophil count < 1 to 0.5 x 10^9/L with fever and/or infection - Absolute neutrophil count < 0.5 x 10^9/L lasting 7 or more days - Platelet count < 50 to 25 x 10^9/L with bleeding - Platelet count < 25 x 10^9/L | Third occurrence | Interrupt JAYPIRCA until recovery to Grade 1 or baseline; restart at 50 mg once daily.
- Grade 3 or greater non-hematologic toxicity a - Absolute neutrophil count < 1 to 0.5 x 10^9/L with fever and/or infection - Absolute neutrophil count < 0.5 x 10^9/L lasting 7 or more days - Platelet count < 50 to 25 x 10^9/L with bleeding - Platelet count < 25 x 10^9/L | Fourth occurrence | Discontinue JAYPIRCA.
Dose modification is not recommended for asymptomatic lymphocytosis. Asymptomatic lipase increase may not necessarily warrant dose modification.
a Evaluate the benefit-risk before resuming treatment at the same dose for a Grade 4 non-hematological toxicity.

2.3 Dosage Modifications for Patients with Severe Renal Impairment

For patients with severe renal impairment (eGFR 15-29 mL/min), reduce the JAYPIRCA dose to 100 mg once daily if the current dose is 200 mg once daily otherwise reduce the dose by 50 mg. If the current dosage is 50 mg once daily, discontinue JAYPIRCA [see Use in Specific Populations (8.7), Clinical Pharmacology (12.3)]. No dosage adjustment of JAYPIRCA is recommended in patients with mild to moderate renal impairment (eGFR 30-89 mL/min).

2.4 Dosage Modifications for Concomitant Use with Strong CYP3A Inhibitors

Avoid concomitant use of strong CYP3A inhibitors with JAYPIRCA [see Drug Interactions (7.1), Clinical Pharmacology (12.3)]. If concomitant use of a strong CYP3A inhibitor is unavoidable, reduce the JAYPIRCA dose by 50 mg. If the current dosage is 50 mg once daily, interrupt JAYPIRCA treatment for the duration of strong CYP3A inhibitor use. After discontinuation of a strong CYP3A inhibitor for 5 half-lives, resume the JAYPIRCA dose that was taken prior to initiating the strong CYP3A inhibitor.

2.5 Dosage Modifications for Concomitant Use with CYP3A Inducers

Avoid concomitant use of strong or moderate CYP3A inducers with JAYPIRCA [see Drug Interactions (7.1), Clinical Pharmacology (12.3)]. If concomitant use with moderate CYP3A inducers is unavoidable and the current dosage of JAYPIRCA is 200 mg once daily, increase the dose to 300 mg. If the current dosage is 50 mg or 100 mg once daily, increase the dose by 50 mg.

3 DOSAGE FORMS AND STRENGTHS

Tablets:

Each 50 mg tablet is blue, arc-triangle shaped, film-coated, and debossed with “Lilly 50” on one side and “6902” on the other side.

Each 100 mg tablet is blue, round, film-coated, and debossed with “Lilly 100” on one side and “7026” on the other side.

4 CONTRAINDICATIONS

None.

5 WARNINGS AND PRECAUTIONS

5.1 Infections

Fatal and serious infections (including bacterial, viral, or fungal infections) and opportunistic infections have occurred in patients treated with JAYPIRCA. Across clinical trials, Grade 3 or higher infections occurred in 25% of 704 patients, most commonly pneumonia (20%), with fatal infections occurring in 5% of patients. Sepsis occurred in 6% of patients and febrile neutropenia in 3.8%. In patients with CLL/SLL, Grade 3 or higher infections occurred in 32% of patients, with fatal infections occurring in 8%. Opportunistic infections after treatment with JAYPIRCA have included, but are not limited to, Pneumocystis jirovecii pneumonia and fungal infection [see Adverse Reactions (6.1)].

Consider prophylaxis, including vaccinations and antimicrobial prophylaxis, in patients who are at increased risk for infections, including opportunistic infections. Monitor patients for signs and symptoms of infection, evaluate promptly, and treat appropriately. Based on severity, reduce dose, temporarily withhold, or permanently discontinue JAYPIRCA [see Dosage and Administration (2.2)].

5.2 Hemorrhage

Fatal and serious hemorrhage has occurred with JAYPIRCA. Major hemorrhage (defined as Grade 3 or higher bleeding or any central nervous system bleeding) occurred in 2.6% of 704 patients treated with JAYPIRCA, including gastrointestinal hemorrhage; fatal hemorrhage occurred in 0.3% of patients. Bleeding of any grade, excluding bruising and petechiae, occurred in 16% of patients [see Adverse Reactions (6.1)].

Major hemorrhage occurred in 0.6% of patients taking JAYPIRCA without antithrombotic agents and 2.0% of patients taking JAYPIRCA with antithrombotic agents. Consider the risks and benefits of antithrombotic agents when co-administered with JAYPIRCA. Monitor patients for signs of bleeding. Based on severity of bleeding, reduce dose, temporarily withhold, or permanently discontinue JAYPIRCA [see Dosage and Administration (2.2)].

Consider the benefit-risk of withholding JAYPIRCA for 3 to 7 days pre- and post-surgery depending upon the type of surgery and risk of bleeding.

5.3 Cytopenias

JAYPIRCA can cause cytopenias, including neutropenia, thrombocytopenia, and anemia.

Across clinical trials, Grade 3 or 4 cytopenias, including decreased neutrophils (27%), decreased platelets (13%), and decreased hemoglobin (11%) developed in patients treated with JAYPIRCA. Grade 4 decreased neutrophils developed in 15% of patients and Grade 4 decreased platelets developed in 6% of patients [see Adverse Reactions (6.1)].

Monitor complete blood counts regularly during treatment. Based on severity, reduce dose, temporarily withhold, or permanently discontinue JAYPIRCA [see Dosage and Administration (2.2)].

5.4 Cardiac Arrhythmias

Cardiac arrhythmias, including atrial fibrillation and atrial flutter, were reported in recipients of JAYPIRCA. Atrial fibrillation or flutter were reported in 3.4% of patients, with Grade 3 or 4 atrial fibrillation or flutter reported in 1.6% of 704 patients across clinical trials [see Adverse Reactions (6.1)]. Other serious cardiac arrhythmias such as supraventricular tachycardia and cardiac arrest occurred in 0.4% of patients. Patients with cardiac risk factors, such as hypertension, or previous arrhythmias may be at increased risk.

Monitor for signs and symptoms of arrhythmias (e.g., palpitations, dizziness, syncope, dyspnea) and manage appropriately. Based on severity, reduce dose, temporarily withhold, or permanently discontinue JAYPIRCA [see Dosage and Administration (2.2)].

5.5 Second Primary Malignancies

Second primary malignancies, including non-skin carcinomas, developed in 9% of 704 patients treated with JAYPIRCA monotherapy across clinical trials. The most frequent malignancy was non-melanoma skin cancer, reported in 4.4% of 704 patients. Other second primary malignancies included solid tumors (including genitourinary and breast cancers) and melanoma. Advise patients to use sun protection and monitor patients for the development of second primary malignancies.

5.6 Hepatotoxicity, Including Drug-Induced Liver Injury

Hepatotoxicity, including severe, life-threatening, and potentially fatal cases of drug-induced liver injury (DILI), has occurred in patients treated with Bruton tyrosine kinase inhibitors, including JAYPIRCA.

Evaluate bilirubin and transaminases at baseline and throughout treatment with JAYPIRCA. For patients who develop abnormal liver tests after JAYPIRCA, monitor more frequently for liver test abnormalities and clinical signs and symptoms of hepatic toxicity. If DILI is suspected, withhold JAYPIRCA. Upon confirmation of DILI, discontinue JAYPIRCA.

5.7 Embryo-Fetal Toxicity

Based on findings in animals, JAYPIRCA can cause fetal harm when administered to a pregnant woman. In animal reproduction studies, administration of pirtobrutinib to pregnant rats during the period of organogenesis caused embryo-fetal toxicity including embryo-fetal mortality and malformations at maternal exposures (AUC) approximately 3-times the recommended dose of 200 mg once daily. Advise pregnant women of the potential risk to a fetus. Advise females of reproductive potential to use effective contraception during treatment with JAYPIRCA and for one week after the last dose [see Use in Specific Populations (8.1, 8.3)].

6 ADVERSE REACTIONS

The following clinically significant adverse reactions are described elsewhere in the labeling:

- Infections [see Warnings and Precautions (5.1)]
- Hemorrhage [see Warnings and Precautions (5.2)]
- Cytopenias [see Warnings and Precautions (5.3)]
- Atrial Fibrillation and Atrial Flutter [see Warnings and Precautions (5.4)]
- Second Primary Malignancies [see Warnings and Precautions (5.5)]
- Hepatotoxicity, including DILI [see Warnings and Precautions (5.6)]

6.1 Clinical Trials Experience

Because clinical trials are conducted under widely varying conditions, adverse reaction rates observed in the clinical trials of a drug cannot be compared to rates in the clinical trials of another drug and may not reflect the rates observed in the general patient population.

The data in the WARNINGS AND PRECAUTIONS reflect exposure to JAYPIRCA as a single-agent, administered at 200 mg once daily in 704 patients with hematologic malignancies in the BRUIN and the BRUIN-CLL-321 studies. Among these 704 patients, the median duration of exposure was 12 months; 65% were exposed for at least 6 months and 50% were exposed for at least one year.

In this pooled safety population, the most common (≥ 30%) adverse reactions, including laboratory abnormalities, were decreased neutrophil count (54%), decreased hemoglobin (43%), decreased leukocytes (32%), fatigue (31%), decreased platelets (31%), decreased lymphocyte count (31%), and calcium decreased (30%)

Mantle Cell Lymphoma

BRUIN

The safety of JAYPIRCA was evaluated in the BRUIN trial, an open-label, multicohort, single-arm study in patients with previously treated MCL who received a prior BTK inhibitor [see Clinical Studies (14.1)]. The trial required a platelet count ≥ 50 x 10^9/L, absolute neutrophil count ≥ 0.75 x 10^9/L, hepatic transaminases ≤ 2.5 times upper limit of normal (ULN), and an ECOG performance status of 0 to 2. The trial excluded patients with active central nervous system (CNS) involvement by lymphoma, significant cardiovascular disease, major bleeding or grade ≥ 3 arrhythmia with a prior BTK inhibitor, prolonged QTc interval, or need for a strong CYP3A inhibitor or inducer or strong P-gp inhibitor.

Patients received JAYPIRCA 200 mg orally once daily until disease progression or unacceptable toxicity (n = 128); 36% were exposed for 6 months or longer and 10% were exposed for at least one year. The median number of prior therapies was 3 (range: 1-9). The median age was 71 years (range: 46 to 88 years) and 80% of patients were male. Race was reported for all patients; 78% were White, 14% were Asian, 2.3% were Black, and 2.3% were Hispanic or Latino.

Serious adverse reactions occurred in 38% of patients who received JAYPIRCA. Serious adverse reactions that occurred in ≥ 2% of patients were pneumonia (14%), COVID-19 (4.7%), musculoskeletal pain (3.9%), hemorrhage (2.3%), pleural effusion (2.3%), and sepsis (2.3%). Fatal adverse reactions within 28 days of the last dose of JAYPIRCA occurred in 7% of patients, most commonly due to infections (4.7%) including COVID-19 (3.1% of all patients).

Adverse reactions led to dose reductions in 4.7%, treatment interruption in 32%, and permanent discontinuation of JAYPIRCA in 9%. Adverse reactions that resulted in dosage modification in > 5% of patients included pneumonia and neutropenia. Adverse reactions which resulted in permanent discontinuation of JAYPIRCA in > 1% of patients included pneumonia.

The most common adverse reactions (≥ 15%), excluding laboratory terms, were fatigue, musculoskeletal pain, diarrhea, edema, dyspnea, pneumonia, and bruising.

Table 2 summarizes select adverse reactions in BRUIN.

Table 2: Adverse Reactions (≥ 10%) in Patients with MCL Who Received JAYPIRCA
 | JAYPIRCA 200 mg once daily
 | N = 128
Adverse Reactionsa | All Grades (%) | Grade 3-4 (%)
General Disorders
Fatigue | 29 | 1.6
Edema | 18 | 0.8
Fever | 13 | -
Musculoskeletal and Connective Tissue Disorders
Musculoskeletal pain | 27 | 3.9
Arthritis or arthralgia | 12 | 0.8
Gastrointestinal Disorders
Diarrhea | 19 | -
Constipation | 13 | -
Abdominal pain | 11 | 0.8
Nausea | 11 | -
Respiratory, thoracic, and mediastinal disorders
Dyspnea | 17 | 2.3
Cough | 14 | -
Injury
Bruising | 16 | -
Infections
Pneumonia | 16 b | 14
Upper respiratory tract infections | 10 | 0.8
Nervous system disorders
Peripheral neuropathy | 14 | 0.8
Dizziness | 10 | -
Skin and subcutaneous disorders
Rash | 14 | -
Vascular disorders
Hemorrhage | 11 c | 3.1
a Each term listed includes other related terms.
b includes 1 fatality from COVID-19 pneumonia.
c includes 1 fatality from hemorrhage.

Clinically relevant adverse reactions in < 10% include vision changes, memory changes, headache, urinary tract infection, herpesvirus infection, and tumor lysis syndrome.

Table 3 summarizes laboratory abnormalities in BRUIN.

Table 3: Select Laboratory Abnormalities (≥ 10%) That Worsened from Baseline in Patients with MCL Who Received JAYPIRCA
Laboratory Abnormality | JAYPIRCAa 200 mg once daily
Laboratory Abnormality | All Grades (%) | Grade 3 or 4 (%)
Hematology
Hemoglobin decreased | 42 | 9
Platelet count decreased | 39 | 14
Neutrophil count decreased | 36 | 16
Lymphocyte count decreased | 32 | 15
Chemistry
Creatinine increased | 30 | 1.6
Calcium decreased | 19 | 1.6
AST increased | 17 | 1.6
Potassium decreased | 13 | 1.6
Sodium decreased | 13 | -
Lipase increased | 12 | 4.4
Alkaline phosphatase increased | 11 | -
ALT increased | 11 | 1.6
Potassium increased | 11 | 0.8
a The denominator used to calculate the rate varied from 90 to 127 based on the number of patients with a baseline value and at least one post-treatment value.

Grade 4 laboratory abnormalities in > 5% of patients included neutrophils decreased (10%), platelets decreased (7%), and lymphocytes decreased (6%).

Lymphocytosis: Upon initiation of JAYPIRCA, a temporary increase in lymphocyte counts (defined as absolute lymphocyte count increased ≥ 50% from baseline and a post-baseline value ≥ 5,000/μL) occurred in 34% of MCL patients in BRUIN. The median time to onset of lymphocytosis was 1.1 weeks, with 75% of cases occurring within 2.1 weeks, and the median duration was 11 weeks.

Chronic Lymphocytic Leukemia/Small Lymphocytic Lymphoma

BRUIN

The safety of JAYPIRCA was evaluated in the BRUIN trial, an open-label, multicohort, single-arm study in 110 patients with relapsed or refractory CLL/SLL, with 98% having received at least two prior lines of systemic therapy including a covalent BTK inhibitor and a BCL-2 inhibitor [see Clinical Studies (14.2)]. The trial required a platelet count ≥ 50 x 10^9/L, absolute neutrophil count ≥ 0.75 x 10^9/L, hepatic transaminases ≤ 2.5 times upper limit of normal (ULN), and an ECOG performance status of 0 to 2. The trial excluded patients with active central nervous system (CNS) involvement by lymphoma, significant cardiovascular disease, major bleeding, uncontrolled or symptomatic arrhythmias, prolonged QTc interval, or need for a strong CYP3A inhibitor or inducer or strong P-gp inhibitor.

Patients received JAYPIRCA 200 mg orally once daily until disease progression or unacceptable toxicity (N = 110); 60% were exposed for at least 1 year and 14% were exposed for at least two years. The median age was 68 years (range: 41 to 88 years) and 67% of patients were male. Race was reported in 110 (100%) patients; of these patients, 89% were White, 4.5% were Black, 1.8% were Asian, and 1.8% were Hispanic or Latino. The median number of prior therapies was 5 (range: 1-11).

Serious adverse reactions occurred in 56% of patients who received JAYPIRCA. Serious adverse reactions that occurred in ≥ 5% of patients were pneumonia (18%), COVID-19 (9%), sepsis (7%), and febrile neutropenia (7%). Fatal adverse reactions within 28 days of the last dose of JAYPIRCA occurred in 11% of patients, most commonly due to infections (10%), including sepsis (5%) and COVID-19 (2.7%).

Adverse reactions led to dose reductions in 3.6%, treatment interruption in 42%, and permanent discontinuation of JAYPIRCA in 9%. Adverse reactions which resulted in dose reductions of JAYPIRCA in > 1% of patients included neutropenia. Adverse reactions which resulted in treatment interruptions of JAYPIRCA in > 5% of patients included pneumonia, neutropenia, febrile neutropenia, and COVID-19. Adverse reactions which resulted in permanent discontinuation of JAYPIRCA in > 1% of patients included second primary malignancy, COVID-19, and sepsis.

The most common adverse reactions (≥ 20%), excluding laboratory terms, were fatigue, bruising, cough, musculoskeletal pain, COVID-19, diarrhea, pneumonia, abdominal pain, dyspnea, hemorrhage, edema, nausea, pyrexia, and headache. Table 4 summarizes select adverse reactions for patients treated on BRUIN.

Table 4: Adverse Reactions (≥ 10%) in Patients with CLL/SLL Who Received JAYPIRCA
 | JAYPIRCA 200 mg once daily
 | N = 110
Adverse Reactions a | All Grades (%) | Grade 3-4 (%)
General Disorders
Fatigue | 36 | 2.7
Edema | 21 | 0
Pyrexia | 20 | 2.7
Injury
Bruising | 36 | 0
Fall | 14 | 0.9
Respiratory, thoracic, and mediastinal disorders
Cough | 33 | 0
Dyspnea | 22 | 2.7
Mucositis | 12 | 0.9
Musculoskeletal and Connective Tissue Disorders
Musculoskeletal pain | 32 | 0.9
Arthritis or arthralgia | 19 | 1.8
Infections
COVID-19 | 28b | 7
Pneumonia | 27c | 16
Upper respiratory tract infections | 13 | 2.7
Respiratory tract infection | 11 | 1.8
Gastrointestinal Disorders
Diarrhea | 26 | 0
Abdominal pain | 25 | 2.7
Nausea | 21 | 0
Constipation | 14 | 0
Vascular disorders
Hemorrhage | 22d | 2.7
Hypertension | 12 | 5
Nervous system disorders
Headache | 20 | 0.9
Peripheral neuropathy | 16 | 3.6
Dizziness | 15 | 0
Neurological changes | 12e | 2.7
Skin and subcutaneous disorders
Rash | 19 | 0.9
Psychiatric disorders
Insomnia | 14 | 0
Neoplasms benign, malignant and unspecified
Second primary malignancy | 13f | 2.7
Renal and urinary disorders
Renal insufficiency | 12g | 6
Metabolism and nutrition disorders
Decreased appetite | 12 | 0
Cardiac disorders
Supraventricular tachycardia | 10h | 5
a Each term listed includes other related terms.
b Includes COVID-19 pneumonia. Includes 1 fatality from COVID-19 and 2 fatalities from COVID-19 pneumonia.
c Includes COVID-19 pneumonia. Includes 2 fatalities from COVID-19 pneumonia and 1 fatality from pneumonia.
d Includes preferred terms hemorrhage, intracranial hemorrhage, and gastrointestinal hemorrhage.
e Includes preferred terms memory impairment, confusional state, encephalopathy, mental status changes.
f Includes preferred terms second primary malignancy and nonmelanoma skin cancers. 1 fatality from metastatic malignant melanoma.
g Includes preferred terms renal failure, chronic kidney disease, acute kidney injury.
h Includes preferred terms supraventricular tachycardia, sinus tachycardia, atrial fibrillation.

Clinically relevant adverse reactions in < 10% include vision changes, lower respiratory tract infection, urinary tract infection, herpesvirus infection, and tumor lysis syndrome.

Table 5 summarizes laboratory abnormalities in BRUIN.

Table 5: Select Laboratory Abnormalities (≥ 20%) That Worsened from Baseline in Patients with CLL/SLL Who Received JAYPIRCA
Laboratory Abnormality | JAYPIRCAa 200 mg once daily
Laboratory Abnormality | All Grades (%) | Grade 3 or 4 (%)
Hematology
Neutrophil count decreased | 63 | 45
Hemoglobin decreased | 48 | 19
Platelet count decreased | 30 | 15
Lymphocyte count decreased | 23 | 8
Chemistry
Calcium decreased | 40 | 2.8
Sodium decreased | 30 | 0
ALT increased | 23 | 2.8
AST increased | 23 | 1.9
Creatinine increased | 23 | 0
Lipase increased | 21 | 7
Alkaline phosphatase increased | 21 | 0
a The denominator used to calculate the rate varied from 83 to 108 based on the number of patients with a baseline value and at least one post-treatment value.

Grade 4 laboratory abnormalities in > 5% of patients included neutrophils decreased (23%).

**Lymphocytosis: Upon initiation of JAYPIRCA, a temporary increase in lymphocyte counts (defined as absolute lymphocyte count increased ≥ 50% from baseline and a post-baseline value ≥ 5,000/μL) occurred in 64% of CLL/SLL patients in BRUIN. The median time to onset of lymphocytosis was 1.1 weeks, with 75% of cases occurring within 1.1 weeks, and the median duration was 19 weeks.

BRUIN-321

The safety of JAYPIRCA was evaluated in BRUIN CLL-321, a randomized, multicenter, open-label active control trial [see Clinical Studies (14.2)]. The trial enrolled patients with relapsed or refractory CLL/SLL who were previously treated with a covalent BTK inhibitor. The trial required a platelet count ≥ 50 x 10^9/L, absolute neutrophil count ≥ 0.75 x 10^9/L, and an estimated creatinine clearance ≥ 30 mL/min. The trial excluded patients with significant cardiovascular disease including uncontrolled or symptomatic arrhythmias, or major bleeding on a prior covalent BTK inhibitor.

The trial enrolled 238 patients who were randomized in a 1:1 fashion to receive JAYPIRCA given orally once daily at a dose of 200 mg until disease progression or unacceptable toxicity or investigator's choice of either idelalisib in combination with a rituximab product or bendamustine in combination with a rituximab product [see Clinical Studies (14.2)]. One hundred sixteen patients received JAYPIRCA and 109 patients received investigator's choice of idelalisib and rituximab or bendamustine and rituximab.

The median duration of treatment with JAYPIRCA was 15 months with 78% on treatment for greater than 6 months and 66% for greater than 12 months.

Serious adverse reactions occurred in 47% of patients who received JAYPIRCA. Serious adverse reactions that occurred in ≥ 3% of patients were pneumonia (21%), COVID-19 (5%), and sepsis (3.4%). Fatal adverse reactions within 30 days of the last dose of JAYPIRCA occurred in 8% of patients, most commonly due to infections (7%), COVID-19 (5%) and pneumonia (3.4%).

Adverse reactions led to permanent discontinuation of JAYPIRCA in 17% of patients, dose reductions in 10%, and treatment interruption in 51%. Adverse reactions which resulted in dose reductions of JAYPIRCA in > 1% of patients included neutropenia. Adverse reactions which resulted in treatment interruptions of JAYPIRCA in > 5% of patients included pneumonia, neutropenia, hemorrhage and COVID-19. Adverse reactions which resulted in permanent discontinuation of JAYPIRCA in > 1% of patients included pneumonia, COVID-19, neutropenia, anemia, and cardiac arrythmias.

The most common adverse reactions (≥ 20%), excluding laboratory terms, were pneumonia and upper respiratory tract infections. Table 6 summarizes select adverse reactions for patients treated on BRUIN CLL-321.

Table 6: Adverse Reactions (≥ 10%) in Patients with CLL/SLL Who Received JAYPIRCA (BRUIN CLL-321)
 | JAYPIRCA |  | Investigator's Choice
 | N = 116 |  | N = 109
Adverse Reactionsa | All Grades (%) | Grade 3-4 (%) | All Grades (%) | Grade 3-4 (%)
Pneumonia | 28b | 16 | 16b | 11
Upper respiratory tract infections | 21 | 0.9 | 10 | 0
COVID-19 | 17c | 0.9 | 19c | 4.6
General Disorders
Fatigue | 19 | 2.6 | 26 | 1.8
Edema | 12 | 0 | 8 | 0
Cough | 19 | 0 | 19 | 0
Fever | 13 | 0.9 | 27 | 0.9
Nausea | 11 | 0.9 | 20 | 0
Headache | 11 | 0.9 | 16 | 0
Hemorrhage | 16 | 2.6 | 7 | 0
Musculoskeletal and Connective Tissue Disorders
Musculoskeletal pain | 19 | 0.9 | 13 | 0
Gastrointestinal Disorders
Diarrhea | 16 | 0 | 31 | 6
Skin and Subcutaneous Disorders
Rash | 14 | 2.6 | 20 | 4.6
a Each term listed includes other related terms.
b Includes COVID-19 pneumonia. Includes 3 fatalities from COVID-19 pneumonia, 3 fatalities from pneumonia, for JAYPIRCA; includes 3 fatalities from pneumonia for IR and 1 fatality from COVID-19 pneumonia for BR.
c Includes COVID-19 pneumonia. Includes 3 fatalities from COVID-19 pneumonia and 3 fatalities from COVID-19 for JAYPIRCA and 1 fatality from COVID-19 for IR and 1 fatality from COVID-19 pneumonia for BR.

Clinically relevant adverse reactions in <10% in patients who received JAYPIRCA include vision changes, urinary tract infection, herpes virus infection, and hypertension.

Table 7 summarizes laboratory abnormalities in BRUIN CLL-321.

Table 7: Select Laboratory Abnormalities (≥ 20%) That Worsened from Baseline in Patients with CLL/SLL Who Received JAYPIRCA (BRUIN CLL-321)
Laboratory Abnormality | JAYPIRCA a |  | Investigator's Choice a
Laboratory Abnormality | All Grades (%) | Grade 3 or 4 (%) | All Grades (%) | Grade 3 or 4 (%)
Hematology
Neutrophil count decreased | 54 | 26 | 67 | 27
Hemoglobin decreased | 45 | 10 | 42 | 8
Platelet count decreased | 37 | 17 | 42 | 9
Chemistry
ALT increased | 25 | 1.8 | 46 | 14
Creatinine increased | 25 | 0 | 20 | 1
Calcium decreased | 23 | 0.9 | 31 | 0
Sodium decreased | 22 | 0.9 | 21 | 1
Bilirubin increased | 21 | 0.9 | 21 | 1
a The denominator used to calculate the rate varied from 113 to 114 in the JAYPIRCA arm and from 29 to 31 for bendamustine plus rituximab, and 75 for idelalisib plus rituximab, based on the number of patients with a baseline value and at least one posttreatment value.

7 DRUG INTERACTIONS

7.1 Effect of Other Drugs on JAYPIRCA

Strong CYP3A Inhibitors

Pirtobrutinib is a CYP3A substrate. Concomitant use of JAYPIRCA with a strong CYP3A inhibitor increased pirtobrutinib systemic exposure [see Clinical Pharmacology (12.3)], which may increase the risk of JAYPIRCA adverse reactions. Avoid concomitant use of strong CYP3A inhibitors during treatment with JAYPIRCA. If concomitant use of strong CYP3A inhibitors is unavoidable, reduce the JAYPIRCA dosage [see Dosage and Administration (2.4)].

Strong or Moderate CYP3A Inducers

Concomitant use of JAYPIRCA with a strong or moderate CYP3A inducer decreased pirtobrutinib systemic exposure [see Clinical Pharmacology (12.3)], which may reduce JAYPIRCA efficacy. Avoid concomitant use of JAYPIRCA with strong or moderate CYP3A inducers. If concomitant use of moderate CYP3A inducers is unavoidable, increase the JAYPIRCA dosage [see Dosage and Administration (2.5)].

7.2 Effect of JAYPIRCA on Other Drugs

Sensitive CYP2C8, CYP2C19, CYP3A, P-gp, or BCRP Substrates

JAYPIRCA is a P-gp inhibitor, a moderate CYP2C8 and BCRP inhibitor, and a weak CYP2C19 and CYP3A inhibitor. Concomitant use of JAYPIRCA with sensitive P-gp, CYP2C8, BCRP, CYP2C19, or CYP3A substrates increased their plasma concentrations [see Clinical Pharmacology (12.3)], which may increase the risk of adverse reactions related to these substrates for drugs which are sensitive to minimal concentration changes. Follow recommendations for sensitive CYP2C8, CYP2C19, CYP3A, P-gp, or BCRP substrates provided in their approved product labeling.

8 USE IN SPECIFIC POPULATIONS

8.1 Pregnancy

Risk Summary

Based on findings from animal studies, JAYPIRCA can cause fetal harm when administered to a pregnant woman. There are no available data on JAYPIRCA use in pregnant women to evaluate for a drug-associated risk. In an animal reproduction study, administration of pirtobrutinib to pregnant rats during organogenesis resulted in adverse developmental outcomes, including structural abnormalities, altered fetal growth, and embryo-fetal mortality, at maternal exposures approximately 3-times those in patients at the recommended daily dose of 200 mg (see Data). Advise pregnant women of the potential risk to a fetus.

The background risk in the U.S. general population of major birth defects is 2% to 4% and of miscarriage is 15% to 20% of clinically recognized pregnancies.

Data

Animal Data

In an embryo-fetal development study in rats, pregnant animals were administered oral doses of pirtobrutinib at up to 500 mg/kg twice daily during the period of organogenesis. Doses ≥ 375 mg/kg twice daily caused decreased fetal body weights and increased incidence of malformations and variations in the urinary tract (including absent or abnormal ureters and kidneys), reproductive tract (malpositioned ovaries and misshapen uterus), and bone (misshapen sternebrae). At 500 mg/kg twice daily, total resorption was observed. At 375 mg/kg twice daily in rats, the maternal systemic exposures (AUC) were approximately 3 times the human exposure at 200 mg once daily.

8.2 Lactation

Risk Summary

There are no data on the presence of pirtobrutinib in human milk or the effects on the breastfed child or milk production. Because of the potential for serious adverse reactions in the breastfed child, advise women not to breastfeed during treatment with JAYPIRCA and for one week after the last dose.

8.3 Females and Males of Reproductive Potential

Based on findings from animal studies, JAYPIRCA can cause fetal harm when administered to a pregnant woman [see Use in Specific Populations (8.1)].

Pregnancy Testing

Verify pregnancy status in females of reproductive potential prior to initiating JAYPIRCA.

Contraception

Females

Advise females of reproductive potential to use effective contraception during treatment with JAYPIRCA and for one week after the last dose.

8.4 Pediatric Use

Safety and effectiveness of JAYPIRCA have not been established in pediatric patients.

8.5 Geriatric Use

Of the patients with MCL who received the 200 mg dose of JAYPIRCA in BRUIN, 93 (78%) were 65 years of age and older and 39 (33%) were 75 years and older [see Clinical Studies (14.1)]. Clinical studies of JAYPIRCA did not include sufficient numbers of patients with MCL who were less than 65 years of age to determine whether older patients respond differently from younger adult patients. Of the patients with CLL/SLL who received the 200 mg once daily dose of JAYPIRCA in BRUIN and BRUIN-321, 220 (65%) were 65 years of age and older and 78 (33%) were 75 years and older [see Clinical Studies (14.2)]. No overall differences in effectiveness were observed between younger and older patients.

In the pooled safety population in patients with hematologic malignancies in BRUIN and BRUIN CLL-321, 467 (66%) were 65 years of age and older, while 181 (26%) were 75 years of age and older. Patients aged 65 years and older experienced higher rates of Grade 3 and higher adverse reactions and serious adverse reactions compared to patients who were less than 65 years of age.

8.6 Renal Impairment

Severe renal impairment (eGFR15-29 mL/min) increases pirtobrutinib exposure [see Clinical Pharmacology (12.3)]. Reduce the JAYPIRCA dosage in patients with severe renal impairment [see Dosage and Administration (2.3)]. No dosage adjustment of JAYPIRCA is recommended in patients with mild (60-89 mL/min) or moderate (30-59 mL/min) renal impairment.

8.7 Hepatic Impairment

No dosage adjustment of JAYPIRCA is recommended in patients with mild hepatic impairment (total bilirubin ≤ upper limit of normal (ULN) and aspartate aminotransferase (AST) > ULN or total bilirubin > 1 to 1.5 × ULN and any AST), moderate hepatic impairment (total bilirubin > 1.5 to 3 × ULN and any AST), or severe hepatic impairment (total bilirubin > 3 × ULN and any AST) [see Clinical Pharmacology (12.3)].

11 DESCRIPTION

Pirtobrutinib is a kinase inhibitor. It is an orally available, small molecule ATP-competitive inhibitor of BTK. The active pharmaceutical ingredient is pirtobrutinib with the molecular formula C22H21F4N5O3 and a molecular weight of 479.44 g/mol. The chemical name for pirtobrutinib is 5-amino-3-{4-[(5-fluoro-2-methoxybenzamido)methyl]phenyl}-1-[(2S)-1,1,1-trifluoropropan-2-yl]-1H-pyrazole-4-carboxamide.

Pirtobrutinib is a white to practically white to yellow to brown solid. The aqueous solubility of pirtobrutinib is considered practically insoluble, or insoluble, across the pH 1 to pH 7 range.

Pirtobrutinib tablets are supplied as 50 mg or 100 mg film-coated, debossed tablets for oral administration. Each tablet contains inactive ingredients of croscarmellose sodium, hypromellose acetate succinate, lactose monohydrate, magnesium stearate, microcrystalline cellulose and silicon dioxide. The tablet film coating material contains FD&C Blue #2, hypromellose, titanium dioxide and triacetin.

12 CLINICAL PHARMACOLOGY

12.1 Mechanism of action

Pirtobrutinib is a small molecule, noncovalent inhibitor of BTK. BTK is a signaling protein of the B-cell antigen receptor (BCR) and cytokine receptor pathways. In B-cells, BTK signaling results in activation of pathways necessary for B-cell proliferation, trafficking, chemotaxis, and adhesion. Pirtobrutinib binds to wild type BTK and BTK harboring C481 mutations, leading to inhibition of BTK kinase activity. In nonclinical studies, pirtobrutinib inhibited BTK-mediated B-cell CD69 expression and inhibited malignant B-cell proliferation. Pirtobrutinib showed dose-dependent anti-tumor activities in BTK wild type and BTK C481S mutant mouse xenograft models.

12.2 Pharmacodynamics

At the recommended dosage of 200 mg once daily, pirtobrutinib trough concentrations exceeded the BTK IC96. BTK occupancy is maintained throughout the dosing interval, regardless of the intrinsic rate of BTK turnover.

Cardiac Electrophysiology

The effect of a single 900 mg dose of pirtobrutinib (equivalent to approximately 2 times higher than the concentrations achieved at steady state at the recommended dosage of 200 mg once daily) on the QTc interval was evaluated in a placebo-controlled and positive-controlled study in 30 healthy subjects. Pirtobrutinib had no clinically meaningful effect on the change in QTcF interval (i.e., > 10 ms) and there was no relationship between pirtobrutinib exposure and change in QTc interval.

12.3 Pharmacokinetics

The pharmacokinetics of pirtobrutinib were characterized in healthy subjects and in patients with cancer. Pirtobrutinib exposure (AUC) and Cmax increases proportionally following single oral doses ranging from 300 mg to 800 mg (1.5 to 4 times the approved recommended dosage) and once daily doses ranging from 25 – 300 mg (0.125 to 1.5 times the recommended dosage). Steady state was achieved within 5 days of once daily dosing, and the mean (CV%) accumulation ratio was 1.63 (26.7%) based on AUC after administration of 200 mg dosages.

Following administration of the recommended dosage, the geometric mean (CV%) steady-state AUC and Cmax of pirtobrutinib were 92705 h*ng/mL (39%) and 6503 ng/mL (25%), respectively. The geometric mean (CV%) AUC0-24 and Cmax of pirtobrutinib on Cycle 1 Day 8 were 81800 h*ng/mL (66.6%) and 3670 ng/mL (89.5%), respectively.

Absorption

The absolute bioavailability of pirtobrutinib after a single oral 200 mg dose is 85.5% (range 75.9% to 90.9%). The median time (range) to reach peak plasma concentration (tmax) is approximately 2 hours (0.833 to 4.15 hours).

Effect of Food

No clinically significant differences in the pharmacokinetics of pirtobrutinib were observed following administration of a high-fat, high-calorie meal (approximately 800 to 1000 calories with 150 calories from protein, 250 calories from carbohydrate, and 500 to 600 calories from fat) to healthy subjects. A high-fat meal decreased the Cmax of pirtobrutinib by 23% and delayed tmax by 1 hour. There was no effect on pirtobrutinib AUC.

Distribution

The mean apparent central volume of distribution of pirtobrutinib is 34.2 L. Human protein binding of pirtobrutinib is 96% and is independent of concentration in vitro. Mean blood-to-plasma ratio is 0.79.

Elimination

The effective half-life of pirtobrutinib is approximately 20 hours and the mean (CV%) apparent clearance is 2.05 L/h (35.7 %).

Metabolism

Pirtobrutinib is primarily metabolized by CYP3A4 and direct glucuronidation by UGT1A8 and UGT1A9, in vitro.

Excretion

Following a single radiolabeled dose of pirtobrutinib 200 mg to healthy subjects, 37% of the dose was recovered in feces (18% unchanged) and 57% in urine (10% unchanged).

Specific Populations

There were no clinically significant differences in the pharmacokinetics of pirtobrutinib based on age (range 22 – 95 years), sex, race/ethnicity (White 84%, Asian 8%), body weight (range 35.7 – 152 kg), mild (total bilirubin ≤ upper limit of normal (ULN) and aspartate aminotransferase (AST) > ULN or total bilirubin > 1 to 1.5 × ULN and any AST), moderate (total bilirubin > 1.5 to 3 × ULN and any AST), or severe (total bilirubin > 3 × ULN and any AST) hepatic impairment. The effect of other races/ethnicities on the pharmacokinetics of pirtobrutinib is unknown.

Patients with Renal Impairment

Following a single 200 mg oral dose, the AUC of pirtobrutinib in subjects with severe renal impairment (eGFR 15-29 mL/min) increased by 62% and mean unbound AUC increased by 68% compared to healthy subjects with normal renal function. There were no clinically significant differences in the pharmacokinetics of pirtobrutinib in subjects with mild (eGFR 60-89 mL/min) or moderate renal impairment (eGFR 30-59 mL/min). The effect of renal impairment requiring dialysis on the pharmacokinetics of pirtobrutinib is unknown.

Drug Interaction Studies

Clinical Studies and Model-Informed Approaches

Strong CYP3A Inhibitors: Co-administration of a single 200 mg dose of pirtobrutinib with itraconazole (strong CYP3A inhibitor) increased AUC of pirtobrutinib by 49%.

Moderate CYP3A Inhibitors: Verapamil and diltiazem (moderate CYP3A inhibitors) are predicted to increase the AUC of pirtobrutinib by 30% and 20%, respectively.

Strong CYP3A inducers: Coadministration of a single 200 mg dose of pirtobrutinib with rifampin (strong CYP3A inducer) decreased the AUC of pirtobrutinib by 71%.

Moderate CYP3A Inducers: Efavirenz and bosentan (moderate CYP3A inducers) are predicted to decrease the AUC of pirtobrutinib by 49% and 27%, respectively.

Gastric Reducing Agents: No clinically significant differences in pirtobrutinib pharmacokinetics were observed when co-administered with omeprazole (a proton pump inhibitor).

P-glycoprotein (P-gp) inhibitors: No clinically significant differences in pirtobrutinib pharmacokinetics were observed when co-administered with itraconazole (P-gp inhibitor).

CYP3A Substrates: Pirtobrutinib increased the AUC and Cmax of orally administered midazolam (sensitive CYP3A substrate) by 70% and 58%, respectively. Pirtobrutinib did not have a clinically meaningful effect on the exposure of intravenously administered midazolam.

CYP2C8 Substrates: Pirtobrutinib increased the AUC and Cmax of repaglinide (sensitive CYP2C8 substrate) by 130% and 98%, respectively.

CYP2C19 Substrates: Pirtobrutinib increased the AUC and Cmax of omeprazole (sensitive CYP2C19 substrate) by 56% and 49%, respectively.

P-gp Substrates: A single 200 mg dose of pirtobrutinib increased the AUC and Cmax of digoxin (sensitive P-gp substrate) by 17% and 51%, respectively. Multiple doses of pirtobrutinib (200 mg daily) further increased the AUC and Cmax of digoxin (sensitive P-gp substrate) up to 35% and 55%, respectively.

BCRP Substrates: Multiple doses of pirtobrutinib (200 mg daily) increased the AUC and Cmax of rosuvastatin (sensitive BCRP substrate) by 140% and 146%, respectively.

CYP1A2 and CYP2C9 Substrates: Pirtobrutinib did not have a clinically meaningful effect on the exposures of caffeine (sensitive CYP1A2 substrate) or S-warfarin (moderate sensitive CYP2C9 substrate).

In Vitro Studies

Cytochrome P450 (CYP) Enzymes: Pirtobrutinib inhibits CYP2C8, CYP2C9, CYP3A, CYP1A2, CYP2B6, CYP2C19, and CYP2D6. Pirtobrutinib induces CYP3A4, CYP3A5, CYP2B6, and CYP2C19.

Transporter Systems: Pirtobrutinib inhibits P-gp and BCRP, but not OAT1, OAT3, OCT1, OCT2, OATP1B1, OATP1B3, MATE1, or MATE2-K. Pirtobrutinib is not a substrate of the hepatic transporters. Pirtobrutinib is a substrate of P-gp and BCRP, but not OCT1, OATP1B1, OATP1B3, or BSEP.

13 NONCLINICAL TOXICOLOGY

13.1 Carcinogenesis, mutagenesis, impairment of fertility

Carcinogenicity studies have not been conducted with pirtobrutinib.

Pirtobrutinib was not mutagenic in a bacterial mutagenicity (Ames) assay. Pirtobrutinib was aneugenic in in vitro micronucleus assays using human peripheral blood lymphocytes. Pirtobrutinib was not genotoxic in an in vivo rat bone marrow micronucleus assay at doses up to 2000 mg/kg.

Studies to assess the effects of pirtobrutinib on fertility have not been conducted. In repeat-dose toxicity studies of up to 3-months duration conducted with pirtobrutinib in rats and dogs, no effects on male or female reproductive organs were identified.

14 CLINICAL STUDIES

14.1 Mantle Cell Lymphoma

The efficacy of JAYPIRCA in patients with MCL was evaluated in BRUIN [NCT03740529], an open-label, international, multicohort, single-arm study of JAYPIRCA as monotherapy. Efficacy was based on 120 patients with MCL treated with JAYPIRCA who were previously treated with a BTK inhibitor. JAYPIRCA was given orally at a dose of 200 mg once daily and was continued until disease progression or unacceptable toxicity. Patients with active central nervous system lymphoma or allogeneic hematopoietic stem cell transplantation (HSCT) or CAR-T cell therapy within 60 days were excluded.

The median age was 71 years (range: 46 to 88 years); 79% were male; 78% were White, 14% Asian, 1.7% Black or African American. Seventy-eight percent of patients had the classic/leukemic variant of MCL, 12% had pleomorphic MCL, and 11% had blastoid MCL. The simplified Mantle Cell Lymphoma International Prognostic Index (sMIPI) score was low in 15%, intermediate in 59%, and high in 26% of patients. Patients received a median number of 3 prior lines of therapy (range: 1 to 9) with 93% having received 2 or more prior lines. All received 1 or more prior lines of therapy containing a BTK inhibitor; other prior therapies included chemoimmunotherapy in 88%, HSCT in 20%, lenalidomide in 18%, and CAR-T therapy in 9%. The most common prior BTK inhibitors received were ibrutinib (67%), acalabrutinib (30%), and zanubrutinib (8%). Patients may have received more than one prior BTK inhibitor; 83% of patients discontinued the last BTK inhibitor for refractory or progressive disease, 10% discontinued for toxicity, and 5% discontinued for other reasons.

Efficacy was based on overall response rate (ORR) and duration of response (DOR), as assessed by an independent review committee (IRC) using 2014 Lugano criteria. Efficacy results are shown in Table 8. Additionally, the Kaplan-Meier estimate for the DOR rate at 6 months was 65.3% (95% CI: 49.8, 77.1).

Table 8: Efficacy Results per IRC in Patients with MCL Previously Treated with a BTK Inhibitor
Outcome | JAYPIRCA 200 mg once daily (N = 120)
Overall Response Rate a,b
ORR, n | 60 (50%)
(95% CI, %) | 41, 59
CR, n | 15 (13%)
PR, n | 45 (38%)
Time to Response
Median (range), months | 1.8 (0.8, 4.2)
Duration of Response c
Number censored, n | 36
Median DOR, months (95% CI) | 8.3 (5.7, NE)
CI, confidence interval; CR, complete response; DOR, duration of response; PR, partial response; NE, not estimable.
a PET-CT scans were utilized in response assessments (in 41% of patients), with the remainder being assessed by CT scans only.
b ORR using CT scan-based assessments in all patients was 48% (95% CI: 38, 57) and CR rate was 13%.
c Based on Kaplan-Meier estimation. Estimated median follow-up was 7.3 months.

14.2 Chronic Lymphocytic Leukemia/Small Lymphocytic Lymphoma

BRUIN

The efficacy of JAYPIRCA in patients with CLL/SLL was evaluated in BRUIN [NCT03740529] an open-label, international, single-arm, multicohort study of JAYPIRCA as monotherapy. Efficacy was based on 108 patients with CLL/SLL treated with JAYPIRCA who were previously treated with at least two prior lines of therapy, including a BTK inhibitor and a BCL-2 inhibitor. JAYPIRCA was given orally at a dose of 200 mg once daily and was continued until disease progression or unacceptable toxicity. The trial required a platelet count ≥ 50 x 10^9/L, absolute neutrophil count ≥ 0.75 x 10^9/L, hepatic transaminases ≤ 2.5 times upper limit of normal (ULN), and an ECOG performance status of 0 to 2. The trial excluded patients with significant cardiovascular disease, major bleeding, uncontrolled or symptomatic arrhythmias, prolonged QTc interval, or need for a strong CYP3A inhibitor or inducer or strong P-gp inhibitor. Patients with active central nervous system (CNS) involvement by lymphoma or allogeneic hematopoietic stem cell transplantation (HSCT) within 60 days were excluded.

The median age was 68 years (range: 41 to 88 years); 69% were male; 89% were White, 4.6% Black or African American, 1.9% Asian and 1.9% were Hispanic or Latino. Baseline ECOG performance status was 0 or 1 in 91% of patients and 48% of patients had Rai stage III or IV disease. Among those patients with central testing available, 42% (37 of 88 patients) had a C481 BTK mutation, 54% (43 of 79 patients) had 17p deletion and/or TP53 mutation, 93% (77 of 83 patients) had unmutated IGHV, and 22% (16 of 72 patients) had 11q deletion. Patients received a median number of 5 prior lines of therapy (range: 2 to 11). The most common prior BTK inhibitors received were ibrutinib (97%), acalabrutinib (9%), and zanubrutinib (0.9%). Seventy-seven percent of patients discontinued the last BTK inhibitor for refractory or progressive disease, 13% discontinued for toxicity, and 10% discontinued for other reasons.

Efficacy was established based on overall response rate (ORR) and duration of response (DOR), as assessed by an independent review committee (IRC) using 2018 iwCLL criteria. Efficacy results are shown in Table 9 -. The median time to response was 3.7 months (range: 1.7, 27.9 months).

Table 9: Efficacy Results per IRC in Patients with CLL/SLL Previously Treated with a BTK Inhibitor and a BCL-2 inhibitor
Outcome | JAYPIRCA 200 mg once daily (N = 108)
Overall Response Rate
ORR, n | 78 (72%)
(95% CI, %) | 63, 80
PR, n | 78 (72%)
Duration of Response a
Median DOR, months (95% CI) | 12.2 (9.3, 14.7)
CI, confidence interval; PR, partial response.
a Based on Kaplan-Meier estimation. Estimated median follow-up was 15.7 months.

BRUIN-CLL-321

The efficacy of JAYPIRCA in patients with covalent BTK-inhibitor pretreated CLL/SLL was evaluated in a randomized, open-label, active-controlled study (BRUIN-CLL-321, NCT 04666038).

The trial randomized 238 patients who were previously treated for CLL/SLL, including a covalent BTK inhibitor. Patients previously treated with a non-covalent BTK inhibitor were not permitted. Patients were randomized in a 1:1 ratio to receive either:

- JAYPIRCA given orally once daily at a dose of 200 mg until disease progression or unacceptable toxicity, or
- Investigator's choice:
  - Idelalisib plus a rituximab product (IR): Idelalisib 150 mg orally twice daily until disease progression or unacceptable toxicity, in combination with 8 infusions of a rituximab product (375 mg/m^2 intravenously on Day 1 of Cycle 1, followed by 500 mg/m^2 every 2 weeks for 4 doses and then every 4 weeks for 3 doses), with a 28-day cycle length.
  - Bendamustine plus a rituximab product (BR): Bendamustine 70 mg/m^2 intravenously (Day 1 and 2 of each 28-day cycle), in combination with a rituximab product (375 mg/m^2 intravenously on Day 1 of Cycle 1, then 500 mg/m^2 on Day 1 of subsequent cycles), for up to 6 cycles.

Crossover to JAYPIRCA monotherapy was permitted for patients in the investigator's choice arm after confirmed disease progression. Of the 119 patients in the investigator's choice arm, 50 crossed over to receive JAYPIRCA therapy.

Randomization was stratified by 17p deletion status and receipt of prior venetoclax treatment. Of the 238 patients randomized, 119 were assigned to JAYPIRCA monotherapy, 82 to IR, and 37 to BR. The median age was 67 years (range: 42 to 90 years); 70% were male; 81% were White, 12% Asian, 2.5% Black or African American, and 4.2% were Hispanic or Latino. Baseline ECOG performance status was 0 or 1 in 93% of patients and 46% of patients had Rai stage III or IV disease. Forty four percent had 17p deletion and/or TP53 mutation, 69% had unmutated IGHV, and 41% had complex karyotype. Patients received a median number of 3 prior lines of therapy (range: 1 to 13); 51% had received prior BCL2-inhibitor therapy. The most common prior BTK inhibitors received were ibrutinib (87%), acalabrutinib (16%), and zanubrutinib (7%). Seventy-one percent of patients discontinued the most recent BTK inhibitor for refractory or progressive disease, 17% discontinued for toxicity, and 10% discontinued for other reasons.

The primary efficacy outcome measure was progression-free survival (PFS), as assessed by an Independent Review Committee (IRC) using 2018 iwCLL criteria. The median duration of follow up at the primary analysis was 6.6 months. Efficacy results for the primary analysis are presented in Table 10 and Figure 1.

Table 10: Efficacy Results per IRC in Patients with CLL/SLL Previously Treated with a BTK Inhibitor (BRUIN CLL-321)
Parameter a | JAYPIRCA 200 mg once daily (N = 119) | Investigator's Choice of Idelalisib + Rituximab Product or Bendamustine + Rituximab Product (N = 119)
Progression-free Survival
Number of Events, n | 45 (38%) | 50 (42%)
Disease Progression | 35 (29%) | 38 (32%)
Death | 10 (8%) | 12 (10%)
Median PFS (95% CI), months b | 11.2 (9.5, 11.4) | 8.7 (7.2, 10.2)
HR (95% CI) c | 0.58 (0.38, 0.89)
P-value d | 0.0105
CI, confidence interval; HR, hazard ratio.
a Efficacy was assessed using the 2018 International Workshop for Chronic Lymphocytic Leukemia (iwCLL) guidelines
b Based on Kaplan-Meier estimation.
c Based on stratified Cox proportional hazards model.
d 2-sided p-value based on stratified log-rank test

Figure 1 Kaplan-Meier Curve of IRC-Assessed PFS in Patients with CLL/SLL Previously Treated with a BTK Inhibitor in BRUIN CLL-321

At the primary analysis for PFS the objective response rate (ORR) as assessed by IRC using 2018 iwCLL criteria, was 31.1% (95% CI 23.0, 40.2) in the JAYPIRCA arm and 29.4% (95% CI 21.4, 38.5) in the investigator choice arm.

At an updated analysis with a median follow-up time of 19.8 months, 38 patients (32%) in the JAYPIRCA arm and 32 patients (27%) in the investigator's choice arm died. The unadjusted HR for overall survival (OS) was 1.09 (95% CI: 0.68, 1.75). The ORR was 48.7% (95% CI 39.5, 58.1) in the JAYPIRCA arm and 38.7% (95% CI 29.9, 48.0) in the investigator choice arm.

16 HOW SUPPLIED/STORAGE AND HANDLING

How Supplied

JAYPIRCA tablets are supplied as follows:

Tablet Strength | Description | Package Configuration | NDC Number
50 mg | Blue, film coated, arc-triangle shaped tablets debossed with “Lilly 50” on one side and “6902” on the other side. | Bottle with child-resistant closure. Each bottle contains 30 tablets. | 0002-6902-30
100 mg | Blue, film coated, round tablets debossed with “Lilly 100” on one side and “7026” on the other side. | Bottle with child-resistant closure. Each bottle contains 60 tablets. | 0002-7026-60

Storage and Handling

Store JAYPIRCA tablets at room temperature 20°C to 25°C (68°F to 77°F); excursions permitted between 15°C and 30°C (59°F and 86°F) ([see USP Controlled Room Temperature]).

17 PATIENT COUNSELING INFORMATION

Advise the patient to read the FDA-approved patient labeling (Patient Information).

Infections

Advise patients that JAYPIRCA can cause serious infections that may be fatal. Advise patients to report any signs or symptoms of infection (e.g., fever, chills, weakness) [see Warnings and Precautions (5.1)].

Hemorrhage

Inform patients to report signs or symptoms of bleeding. Inform patients that JAYPIRCA may need to be interrupted for major surgeries [see Warnings and Precautions (5.2)].

Cytopenias

Advise patients of the need for periodic monitoring of blood counts during treatment with JAYPIRCA [see Warnings and Precautions (5.3)].

Cardiac Arrhythmias

Counsel patients to report any signs of palpitations, dizziness, fainting, chest discomfort, and shortness of breath [see Warnings and Precautions (5.4)].

Second Primary Malignancies

Inform patients that other malignancies have been reported in patients who have been treated with JAYPIRCA, including skin cancer and other solid tumors. Advise patients to use sun protection and to have monitoring for development of other cancers [see Warnings and Precautions (5.5)].

Hepatotoxicity, Including Drug-Induced Liver Injury

Inform patients that liver problems, including severe, life-threatening, or fatal hepatitis, drug-induced liver injury and abnormalities in liver tests, may develop during JAYPIRCA treatment. Advise patients to contact their healthcare provider immediately if they experience abdominal discomfort, dark urine, or jaundice [see Warnings and Precautions (5.6)].

Embryo-Fetal Toxicity

Advise pregnant women and females of reproductive potential of the potential risk to a fetus. Advise females of reproductive potential to inform their healthcare provider of a known or suspected pregnancy [see Warnings and Precautions (5.7), Use in Specific Populations (8.1, 8.3)].

Advise females of reproductive potential to use effective contraception during treatment with JAYPIRCA and for one week after the last dose [see Use in Specific Populations (8.3)].

Lactation

Advise women not to breastfeed during treatment with JAYPIRCA and for one week after the last dose [see Use in Specific Populations (8.2)].

Administration

Inform patients to take JAYPIRCA orally once daily at approximately the same time each day with or without food and how to make up a missed dose. Advise patients to swallow tablets whole with water. Advise patients not to cut, crush, or chew tablets [see Dosage and Administration (2.1)].

Marketed by: Lilly USA, LLC, Indianapolis, IN 46285, USA

Copyright © 2023, 2025, Eli Lilly and Company. All rights reserved.

JAY-0005-USPI-20251203

PATIENT INFORMATION
JAYPIRCA® (JAY-PIHR-KAA)
pirtobrutinib
tablets

What is JAYPIRCA?
JAYPIRCA is a prescription medicine used to treat adults with:

- mantle cell lymphoma (MCL) that has come back or did not respond to previous treatment and who have already received at least 2 treatments for their cancer, including a Bruton tyrosine kinase (BTK) inhibitor medicine.
- chronic lymphocytic leukemia (CLL) or small lymphocytic lymphoma (SLL) that has come back or did not respond to previous treatment and who have already been treated with a BTK inhibitor for their cancer.

It is not known if JAYPIRCA is safe and effective in children.

Before taking JAYPIRCA, tell your healthcare provider about all of your medical conditions, including if you:

- have an infection or have been advised that you are at increased risk of infection
- have had recent surgery or plan to have surgery. Your healthcare provider may stop JAYPIRCA for any planned medical, surgical, or dental procedure.
- have bleeding problems or are taking a blood thinner medicine
- have or had heart rhythm problems
- have high blood pressure
- have a history of other cancers including skin cancer
- have kidney problems
- have liver problems
- are pregnant or plan to become pregnant. JAYPIRCA can harm your unborn baby.
  Females who are able to become pregnant:
  - Your healthcare provider will do a pregnancy test before starting treatment with JAYPIRCA.
  - You should use effective birth control (contraception) during treatment with JAYPIRCA and for 1 week after your last dose of JAYPIRCA.
  - Tell your healthcare provider right away if you become pregnant or think you are pregnant during treatment with JAYPIRCA.
- are breastfeeding or plan to breastfeed. It is not known if JAYPIRCA passes into your breast milk. Do not breastfeed during treatment with JAYPIRCA and for 1 week after your last dose of JAYPIRCA.

Tell your healthcare provider about all the medicines you take, including prescription and over-the-counter medicines, vitamins, and herbal supplements. Taking JAYPIRCA with certain other medicines may affect how JAYPIRCA or the other medicines work and can cause side effects.

How should I take JAYPIRCA?

- Take JAYPIRCA exactly as your healthcare provider tells you.
- Do not change your dose or stop taking JAYPIRCA unless your healthcare provider tells you to do so.
- Take JAYPIRCA 1 time each day at about the same time each day.
- Take JAYPIRCA with or without food.
- Swallow JAYPIRCA whole with water. Do not cut, crush, or chew the tablets.
- If you miss a dose of JAYPIRCA, take it as soon as you remember on the same day. If it has been more than 12 hours from the time you usually take JAYPIRCA, skip the missed dose, and take your next dose on the next day at your usual time.

What are the possible side effects of JAYPIRCA?
JAYPIRCA can cause serious side effects, including:

- Infections can happen during treatment with JAYPIRCA. These infections can be serious and may lead to death. Your healthcare provider may prescribe vaccines and certain medicines if you have an increased risk of getting infections. Tell your healthcare provider right away if you develop fever, chills, weakness, flu-like symptoms, or any other signs of infection during treatment with JAYPIRCA.
- Bleeding problems (hemorrhage) can happen during treatment with JAYPIRCA and can be serious and may lead to death. Your risk of severe bleeding may increase if you are also taking a blood thinner medicine. Tell your healthcare provider if you develop any signs or symptoms of bleeding, including:
  - blood in your stools or black stools (looks like tar)
  - pink or brown urine
  - unexpected bleeding, or bleeding that is severe or you cannot control
  - vomit blood or vomit blood that looks like coffee grinds
  - cough up blood or blood clots
  - increased bruising
  - dizziness
  - weakness
  - confusion
  - changes in your speech
  - headache that lasts a long time
- Decrease in blood cell counts. Decrease in blood cell counts (white blood cells, platelets, and red blood cells) are common with JAYPIRCA, but can also be severe. This may increase your risk of infection, bleeding, and anemia. Your healthcare provider should do blood tests to check your blood counts regularly during treatment with JAYPIRCA.
- Heart rhythm problems. Heart rhythm problems including atrial fibrillation and atrial flutter have happened in people treated with JAYPIRCA. Your risk for heart rhythm problems may be increased if you have high blood pressure or have had heart rhythm problems in the past. Tell your healthcare provider if you develop any of the following signs or symptoms:
  - fast or irregular heartbeat (palpitations)
  - dizziness
  - fainting
  - chest discomfort
  - shortness of breath
- Second primary cancers. New cancers have happened in people during treatment with JAYPIRCA, including cancers of the skin or other organs. Your healthcare provider will check you for other cancers during treatment with JAYPIRCA. Use sun protection when you are outside in sunlight.
- Liver Problems. Liver problems, which may be severe or life-threatening, or lead to death, can happen in people treated with JAYPIRCA. Your healthcare provider will do blood tests to check your liver before and during treatment with JAYPIRCA. Tell your healthcare provider or get medical help right away if you have any signs of liver problems, including stomach pain or discomfort, dark-colored urine, or yellow skin and eyes.

Your healthcare provider may decrease your dose, temporarily stop, or permanently stop treatment with JAYPIRCA if you develop severe side effects.
The most common side effects of JAYPIRCA include:

- decreased white blood cell count
- decreased red blood cell count
- tiredness

- decreased platelet count
- decreased calcium

These are not all the possible side effects of JAYPIRCA.
Call your doctor for medical advice about side effects. You may report side effects to FDA at 1-800-FDA-1088.

How should I store JAYPIRCA?

- Store JAYPIRCA at room temperature between 68°F to 77°F (20°C to 25°C).
- JAYPIRCA comes in a bottle with a child-resistant cap.

Keep JAYPIRCA and all medicines out of the reach of children.

General information about the safe and effective use of JAYPIRCA.
Medicines are sometimes prescribed for purposes other than those listed in a Patient Information leaflet. Do not use JAYPIRCA for a condition for which it was not prescribed. Do not give JAYPIRCA to other people, even if they have the same symptoms that you have. It may harm them. You can ask your pharmacist or healthcare provider for information about JAYPIRCA that is written for health professionals.

What are the ingredients in JAYPIRCA?
Active ingredient: pirtobrutinib
Inactive ingredients: croscarmellose sodium, hypromellose acetate succinate, lactose monohydrate, magnesium stearate, microcrystalline cellulose, and silicon dioxide. The tablet film coating contains FD&C Blue #2, hypromellose, titanium dioxide, and triacetin.
Marketed by Lilly USA, LLC, Indianapolis, IN 46285, USA
JAYPIRCA is a registered trademark of Eli Lilly and Company.
Copyright © 2023, 2025, Eli Lilly and Company. All rights reserved.
JAY-0005-PPI-20251203
For more information, go to www.jaypirca.com or call 1-800-LillyRx (1-800-545-5979).

This Patient Information has been approved by the U.S. Food and Drug Administration.

Revised: 12/2025

PACKAGE LABEL

PACKAGE LABEL – JAYPIRCA 50 mg Tablets, 30 count bottle

NDC 0002-6902-30

30 tablets Rx only

Jaypirca®

(pirtobrutinib)
tablets

50 mg

Each tablet contains 50 mg pirtobrutinib

www.jaypirca.com

Lilly

PACKAGE LABEL

PACKAGE LABEL – JAYPIRCA 100 mg Tablets, 60 count bottle

NDC 0002-7026-60

60 tablets Rx only

Jaypirca®

(pirtobrutinib)
tablets

100 mg

Each tablet contains 100 mg pirtobrutinib

www.jaypirca.com

Lilly